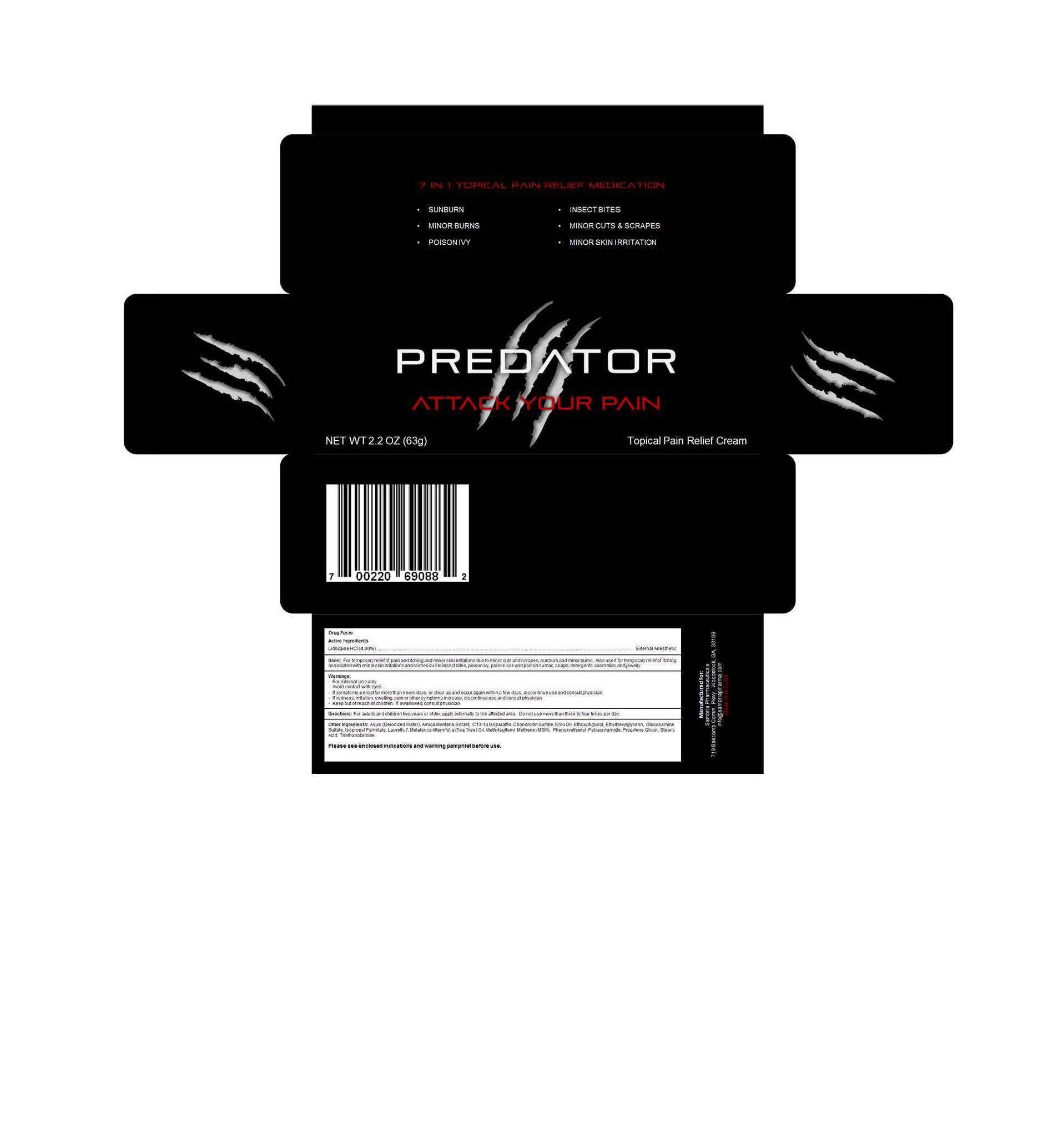 DRUG LABEL: Predator
NDC: 54723-101 | Form: CREAM
Manufacturer: Sambria Pharmaceuticals, LLC
Category: otc | Type: HUMAN OTC DRUG LABEL
Date: 20130313

ACTIVE INGREDIENTS: LIDOCAINE HYDROCHLORIDE 400 mg/1 mg
INACTIVE INGREDIENTS: WATER; ARNICA MONTANA FLOWER; C13-14 ISOPARAFFIN; CHONDROITIN SULFATE (BOVINE); EMU OIL; DIETHYLENE GLYCOL MONOETHYL ETHER; ETHYLHEXYLGLYCERIN; GLUCOSAMINE SULFATE; ISOPROPYL PALMITATE; LAURETH-7; TEA TREE OIL; DIMETHYL SULFONE; PHENOXYETHANOL; POLYACRYLAMIDE (10000 MW); PROPYLENE GLYCOL; STEARIC ACID; TRIETHANOLAMINE BENZOATE

Predator

WARNINGS

For external use only

Avoid contact with eyes

If symptoms persist for more than seven days, or clear up and occur again within a few days, discontinue use and consult physician

If redness, irritation, swelling, pain or ot5her symptoms increase, discontinue use and consult physician

If swallowed consult physician.

active ingredients

lidocaine HCL 4%

Other ingredients

Aqua, Amica Montana Extract, C13-14 Isoparafin, Chondrotin Sulfate, Emu Oil, Ethoxydiglycol, Ethylhexylglycerin, Glucosamine Sulfate, Isopropyl Palmitate, Laureth 7, Melaleuca Alternifoil (Tea Tree) oil, Methylsulfonylmethana (MSM), Phenoxyethanol, Polyacrylamide, Propylene Glycol, Stearic Acid, Triethanolamine

Keep out of reach of children

PURPOSE

External anesthetic

DOSAGE AND ADMINISTRATION

For adults and children two years or older, apply externally to the affected area. Do not use more than three to four times per day.

Uses

For temporary relief of pain and itching and minor skin irratations due to minor cuts and scrapes, sunburn and minor burns. Also used for temporary relief of itching associated with minor skin irritations and rashes due to insect bites, poison ivy, poison oak and poison sumac, soaps, detergetns, cosmetics and jewelry.